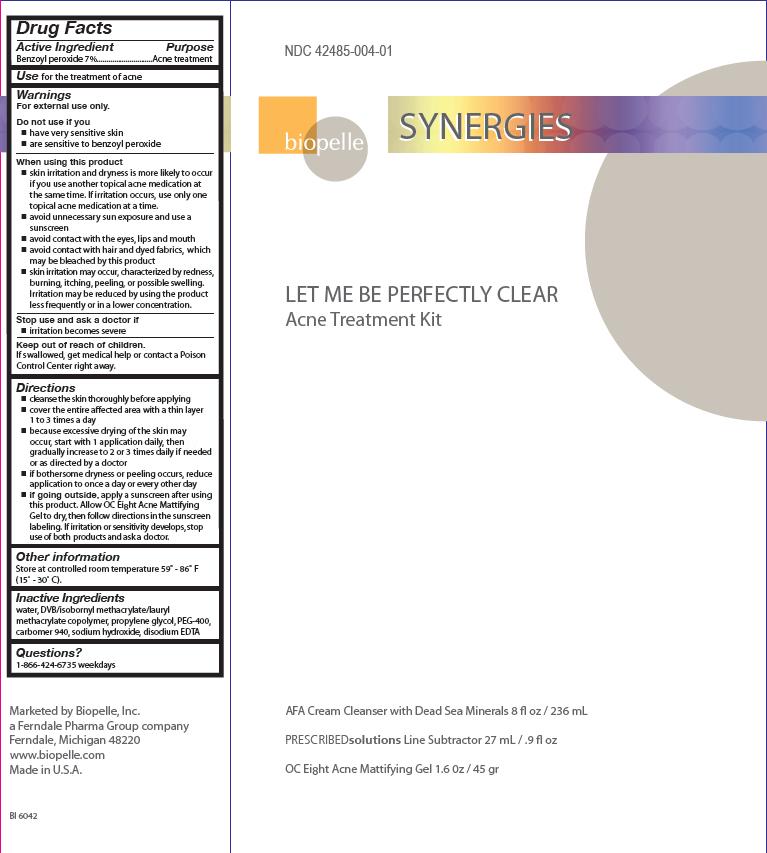 DRUG LABEL: LET ME BE PERFECTLY CLEAR
NDC: 42485-004 | Form: KIT | Route: TOPICAL
Manufacturer: Biopelle, Inc.
Category: otc | Type: HUMAN OTC DRUG LABEL
Date: 20110711

ACTIVE INGREDIENTS: BENZOYL PEROXIDE 7 mg/1 g
INACTIVE INGREDIENTS: WATER; PROPYLENE GLYCOL; CARBOMER HOMOPOLYMER TYPE C; SODIUM HYDROXIDE; EDETATE DISODIUM

LET ME BE PERFECTLY CLEAR Acne Treatment Kit

Active Ingredient

Benzoyl peroxide 7%

Purpose

Acne Treatment

Use

for the treatment of acne

Warnings

For external use only.

Do not use if you

- have very sensitive skin
- are sensitive to benzoyl peroxide

When using this product

- skin irritation and dryness is more likely to occur if you use another topical acne medication at the same time. If irritation occurs, use only one topical acne medication at a time.
- avoid unnecessary sun exposure and use a sunscreen
- avoid contact with the eyes, lips and mouth
- avoid contact with hair and dyed fabrics, which may be bleached by this product
- skin irritation may occur, characterized by redness, burning, itching, peeling, or possible swelling. Irritation may be reduced by using the product less frequently or in a lower concentration.

Stop use and ask a doctor if

- irritation becomes severe

Keep out of reach of children.

If swallowed, get medical help or contact a Poison Control Center right away.

Directions

- cleanse the skin thoroughly before applying
- cover the entire affected area with a thin layer 1 to 3 times a day
- because excessive drying of th skin may occur, start with 1 application daily, then gradually increase to 2 or 3 times daily if needed or as directed by a doctor
- if bothersome dryness or peeling occurs, reduce application to once a day or every other day
- if going outside, apply a sunscreen after using this product. Allow OC Eight Acne Mattifying Gel to dry, then follow directions in the sunscreen labeling. If irritation or sensitivity develops, stop use of both products and ask a doctor.

Other Information

Store at controlled room temperature 59° - 86° F (15° - 30° C).

Inactive Ingredients

water, DVB/isobornyl methacrylate/lauryl methacrylate copolymer, propylene glycol, PEG-400, carbomer 940, sodium hydroxide, disodium EDTA

Questions?

1-866-424-6735 weekdays

Package Label

LET ME BE PERFECTLY CLEAR Acne Treatment Kit NDC 42485-004-01

AFA Cream Cleanser with Dead Sea Minerals 8 fl oz / 236 mL

PRESCRIBEDsolutions Line Subtractor 27 mL / .9 fl oz

OC Eight® Acne Mattifying Gel 1.6 oz / 45 g

Marketed by Biopelle, Inc.
A Ferndale Pharma Group company
Ferndale, Michigan 48220
www.biopelle.com